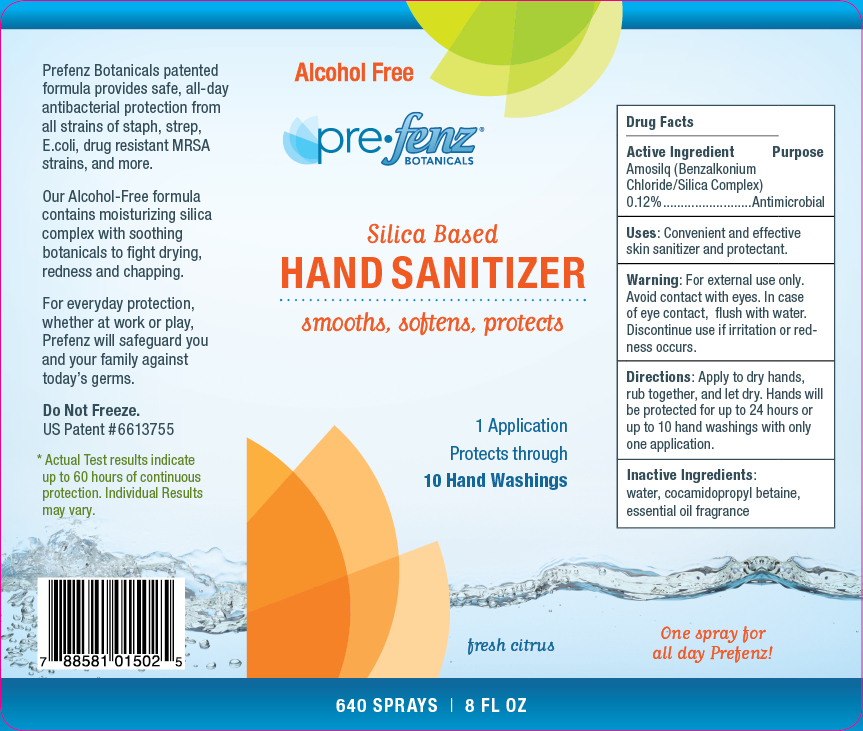 DRUG LABEL: Prefenz Silica Based Hand Sanitizer
NDC: 48404-106 | Form: LIQUID
Manufacturer: Prefense LLC
Category: otc | Type: HUMAN OTC DRUG LABEL
Date: 20100615

ACTIVE INGREDIENTS: BENZALKONIUM CHLORIDE 12 mL/100 mL
INACTIVE INGREDIENTS: WATER; COCAMIDOPROPYL BETAINE; CITRIC ACID MONOHYDRATE

Active Ingredient

Active Ingredient Purpose

Amosliq (Benzalkonium Chloride/Silica Complex) Antimicrobial

0.12%

Uses

Uses: Convenient and effective skin sanitizer and protectant.

Warnings

Warning: For external use only. Avoid contact with eyes. In case of eye contact, flush with water. Discontinue use if irritation or redness occurs.

Directions

Directions: Apply to hands, rub together, and let dry. Hands will be protected for up to 24 hours or up to 10 hand washings with only one application.

Inactive Ingredients

Inactive Ingredients: Water, cocamidopropyl betaine, essential oil fragrance

Package Label

Alcohol Free PreFenz Botanicals Silica Based Hand Sanitizer Smooths, softens, protects 1 Application protects through 10 Hand Washings One spray for all day Prefenz Fresh Citrus.

Prefenz Botanicals patented formula provides safe, all-day antibacterial protection for all strains of staph, strep, E.coli, drug resistant MRSA strains, and more. Our Alcohol-Free formula contains moisturizing silica complex with soothing botanicals to fight drying, redness and chapping. For everyday protection, whether at work or play, Prefenz will safeguard you and your family against today's germs. Do Not Freeze. US Patent #6613755. Actual Test results indicate up to 60 hours of continuous protection. Individual results may vary.